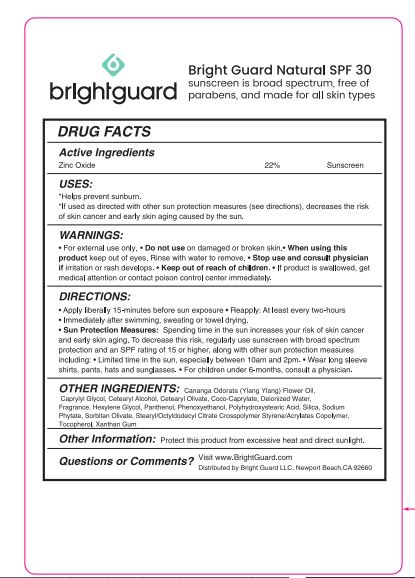 DRUG LABEL: Bright Guard Natural SPF 30
NDC: 76348-676 | Form: LOTION
Manufacturer: Renu Laboratories, LLC
Category: otc | Type: HUMAN OTC DRUG LABEL
Date: 20250512

ACTIVE INGREDIENTS: ZINC OXIDE 209 g/950 g
INACTIVE INGREDIENTS: PHYTATE SODIUM; XANTHAN GUM; SILICON DIOXIDE; PANTHENOL; WATER; SORBITAN OLIVATE; YLANG-YLANG OIL; STYRENE/ACRYLAMIDE COPOLYMER (MW 500000); CAPRYLYL GLYCOL; PHENOXYETHANOL; HEXYLENE GLYCOL; COCO-CAPRYLATE; POLYHYDROXYSTEARIC ACID (2300 MW); CETEARYL OLIVATE; CETOSTEARYL ALCOHOL; ALPHA-TOCOPHEROL ACETATE; STEARYL/OCTYLDODECYL CITRATE CROSSPOLYMER

Bright Guard Natural SPF 30

STATEMENT OF IDENTITY

Bright Guard Natural SPF 30

Active Ingredients

Zinc Oxide 22%

Purpose

Sunscreen

USES:

- Helps prevent sunburn
- If used as directed with other sun protection measures (see directions)‚ decreases the risk of skin cancer and early skin aging caused by the sun.

WARNINGS:

- For external use only
- Do not use on damaged or broken skin
- When using this product keep out of eyes· Rinse with water to remove
- Stop use and consult physician if irritation or rash develops
- Keep out of reach of children
- If product is swallowed‚ get medical attention or contact poison control center immediately

Keep out of reach of children

If product is swallowed, get medical attention or contact poison control center immediately

DIRECTIONS:

- Apply liberally 15 minutes before sun exposure
- Reapply at least every two hours and
- Immediately after swimming, sweating or towel drying
- Sun Protection Measures: Spending time in the sun increases your risk of skin cancer and early skin aging. To decrease this risk‚
  regularly use sunscreen with broad spectrum protection and an SPF rating of 15 or higher, along with other sun protection measures including:
- Limited time in the sun‚ especially between 10am and 2pm
- Wear long sleeve shirts, pants, hats and sunglasses
- For children under 6 months consult a physician

INACTIVE INGREDIENT

OTHER INGREDIENTS:

Cananga Odorata (Ylang Ylang) Flower Oil, Caprylyl Glycol, Cetearyl Alcohol, Cetearyl Olivate, Coco Caprylate, Deionized Water, Fragrance, Hexylene Glycol, Panthenol, Phenoxyethanol, Polyhydroxystearic Acid, Silica, Sodium Phytate, Sorbitan Olivate, Stearyl/Octyldodecyl Citrate Crosspolymer, Styrene / Acrylates Copolymer, Tocopherol, Xanthan Gum

Other Information :

Protect this product from excessive heat and direct sunlight

Questions or Comments ?

Visit www.BrightGuard.com

Distributed by Bright Guard LLC, Newport Beach CA 92660

BRIGHTGUARD NATURAL POUCH LABEL